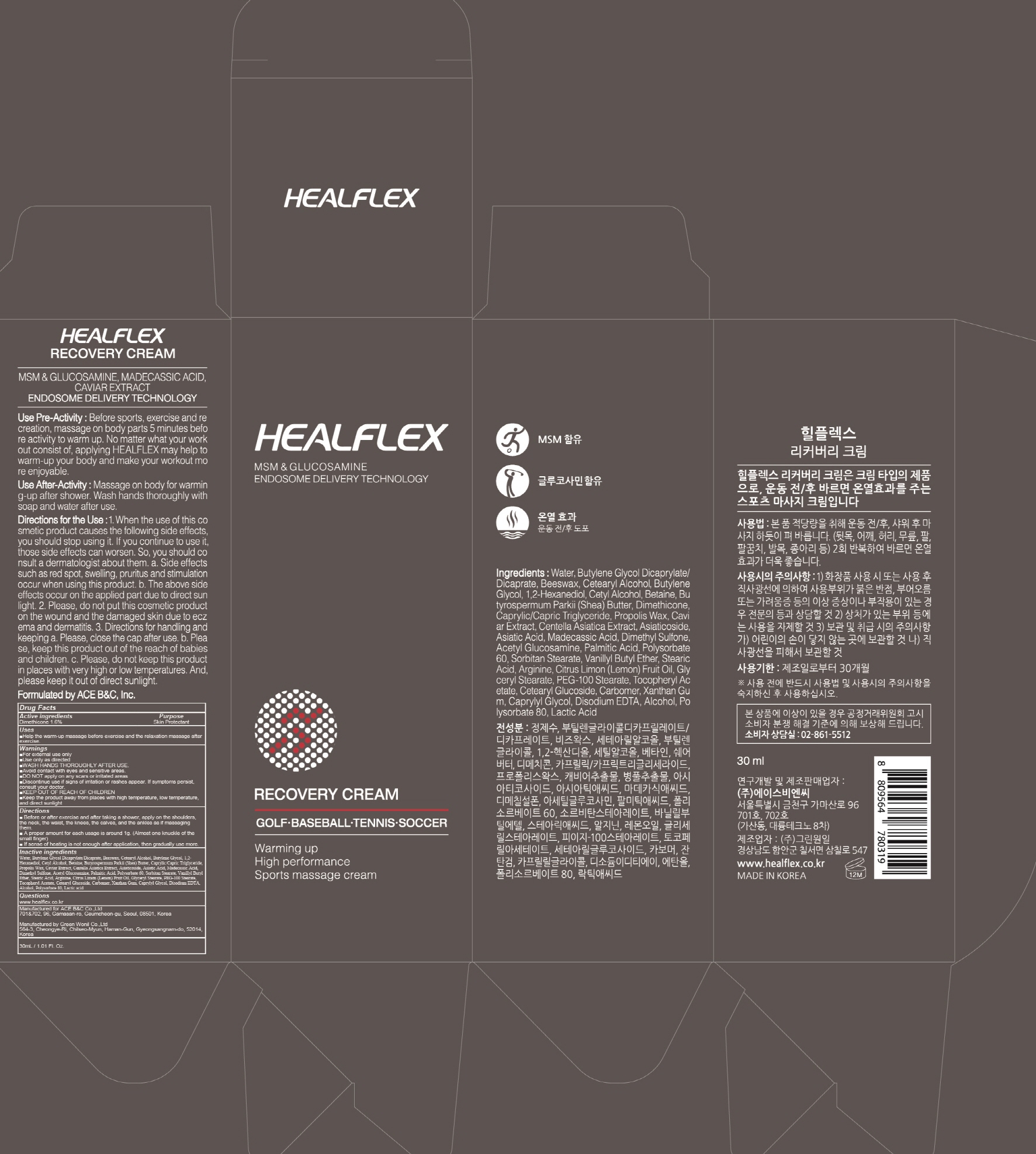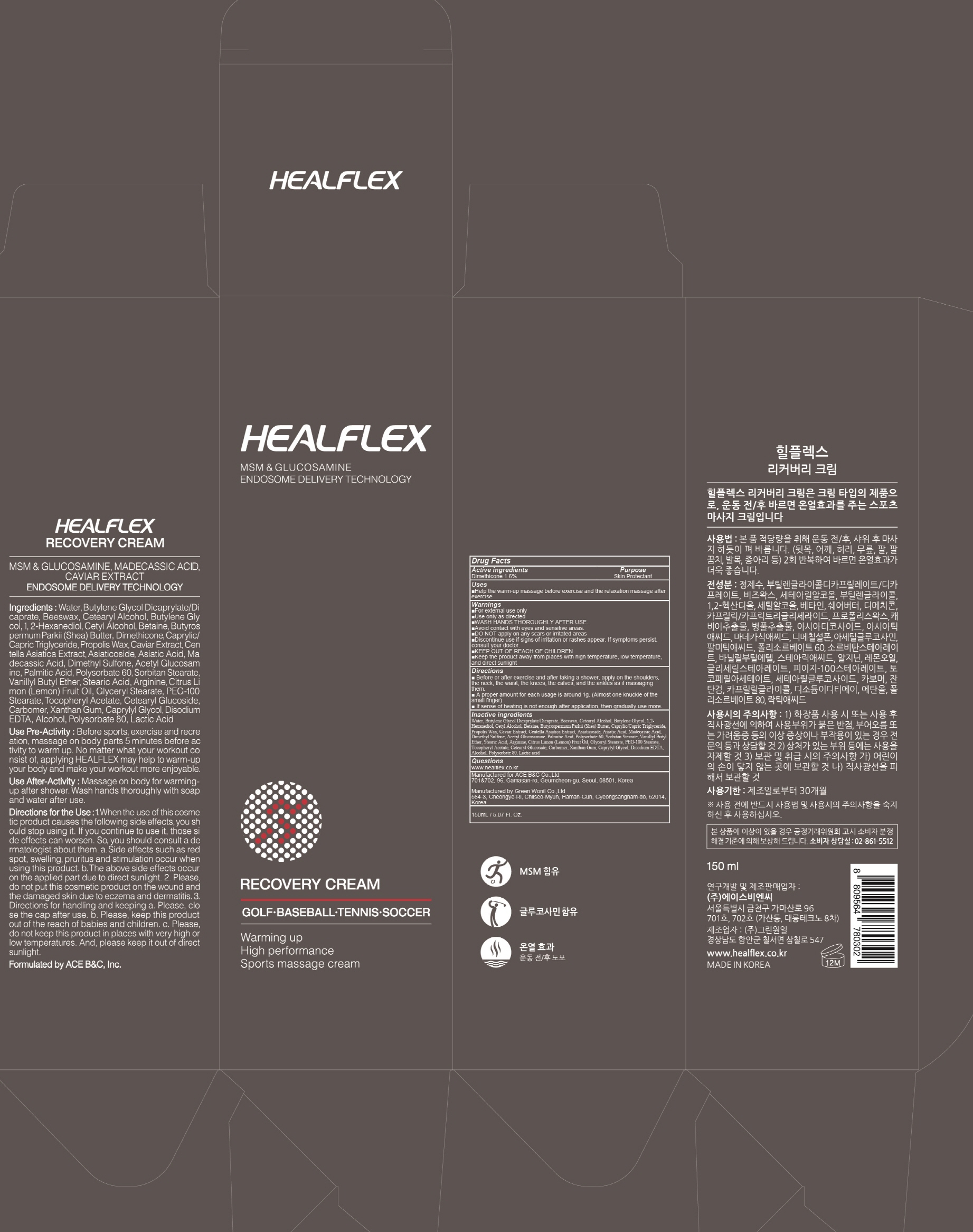 DRUG LABEL: HEALFLEX RECOVERY
NDC: 72504-010 | Form: CREAM
Manufacturer: Ace B&C Co.,Ltd
Category: otc | Type: HUMAN OTC DRUG LABEL
Date: 20180817

ACTIVE INGREDIENTS: Dimethicone 1.6 g/100 mL
INACTIVE INGREDIENTS: Water; Butylene Glycol

ACTIVE INGREDIENT

Active ingredients: Dimethicone 1.6%

INACTIVE INGREDIENT

Inactive ingredients:

Water, Butylene Glycol Dicaprylate/Dicaprate, Beeswax, Cetearyl Alcohol, Butylene Glycol, 1,2-Hexanediol, Cetyl Alcohol, Betaine, Butyrospermum Parkii (Shea) Butter, Caprylic/Capric Triglyceride, Propolis Wax, Caviar Extract, Centella Asiatica Extract, Asiaticoside, Asiatic Acid, Madecassic Acid, Dimethyl Sulfone, Acetyl Glucosamine, Palmitic Acid, Polysorbate 60, Sorbitan Stearate, Vanillyl Butyl Ether, Stearic Acid, Arginine, Citrus Limon (Lemon) Fruit Oil, Glyceryl Stearate, PEG-100 Stearate, Tocopheryl Acetate, Cetearyl Glucoside, Carbomer, Xanthan Gum, Caprylyl Glycol, Disodium EDTA, Alcohol, Polysorbate 80, Lactic acid

PURPOSE

Purpose: Skin Protectant

WARNINGS

- For external use only

- Use only as directed

- WASH HANDS THOROUGHLY AFTER USE.

- Avoid contact with eyes and sensitive areas.

- DO NOT apply on any scars or irritated areas

- Discontinue use if signs of irritation or rashes appear. If symptoms persist, consult your doctor.

- KEEP OUT OF REACH OF CHILDREN

- Keep the product away from places with high temperature, low temperature, and direct sunlight

KEEP OUT OF REACH OF CHILDREN

Uses

Help the warm-up massage before exercise and the relaxation massage after exercise.

Directions

- Before or after exercise and after taking a shower, apply on the shoulders, the neck, the waist, the knees, the calves, and the ankles as if massaging them.

- A proper amount for each usage is around 1g. (Almost one knuckle of the small finger)

- If sense of heating is not enough after application, then gradually use more.